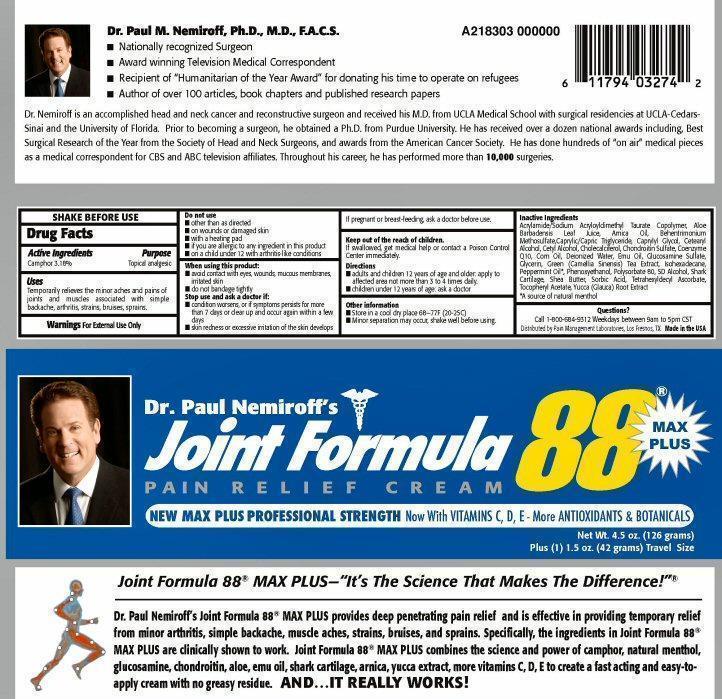 DRUG LABEL: Joint Formula 88 MAX PLUS
NDC: 67676-002 | Form: CREAM
Manufacturer: Sarati International, Inc.
Category: otc | Type: HUMAN OTC DRUG LABEL
Date: 20231027

ACTIVE INGREDIENTS: CAMPHOR (SYNTHETIC) 3.18 g/100 g
INACTIVE INGREDIENTS: SODIUM ACRYLOYLDIMETHYLTAURATE; ALOE VERA LEAF; ARNICA MONTANA; BEHENTRIMONIUM METHOSULFATE; MEDIUM-CHAIN TRIGLYCERIDES; CAPRYLYL GLYCOL; CETOSTEARYL ALCOHOL; CETYL ALCOHOL; CHOLECALCIFEROL; CHONDROITIN SULFATE (BOVINE); UBIDECARENONE; CORN OIL; WATER; EMU OIL; GLUCOSAMINE SULFATE; GLYCERIN; GREEN TEA LEAF; ISOHEXADECANE; PEPPERMINT OIL; PHENOXYETHANOL; POLYSORBATE 80; ALCOHOL; SHARK, UNSPECIFIED; SHEA BUTTER; SORBIC ACID; TETRAHEXYLDECYL ASCORBATE; .ALPHA.-TOCOPHEROL ACETATE; YUCCA GLAUCA ROOT

Joint Formula 88 Max Plus

Drug Facts Active Ingredients

SHAKE BEFORE USE

Camphor 3.18%

Purpose

Topical analgesic

Keep out of reach of children

Keep out of the reach of children.

If swallowed, get medical help or contact a Poison Control Center immediately

Uses

Temporarily relieves the minor aches and pains of joints and muscles associated with simple backache, arthritis, strains, bruises, sprains.

Warnings

For External Use Only

Do not use

- other than as directed
- on wounds or damaged skin
- with a heating pad
- if you are allergic to any ingredient in this product
- on a child under 12 with arthritis-like conditions

When using this product:

- avoid contact with eyes, wounds, mucus membranes, irritated skin
- do not bandage tightly

stop use and ask a doctor if:

- condition worsens, or if symptoms persists for more than 7 days or clears up and occurs again within a few days
- skin redness or excessive irritation of the skin develops

Pregnant or breast-feeding

If pregnant or breast-feeding, ask a doctor before use.

Directions

- adults and children 12 years of age and older: apply to affected area not more than3 to 4 times daily.
- children under 12 years of age: ask a doctor

Other information

- Store in a cool dry place 68 - 77 F (20 - 25 C)
- Minor separation may occur, shake well before using.

Inactive ingredients

Acrylamide/Sodium Acryloydimethyl Taurate Copolymer, Aloe Barbadensis Leaf Juice, Amica Oil, Behentrimonium Methosulfate, Caprylic/Capric Trigyceride, Caprylyl Glycol, Cetearyl Alcohol, Cetyl Alcohol, Cholecalciferol, Chondroitin Sulfate, Coenzyme Q 10, Corn Oil, Deionized Water, Emu Oil, Glucosamine Sulfate, Glycerin, Green (Camellia Sinensis) Tea Extract, Isohexadecane, Peppermint Oil*, Phenoxyethanol, Polysorbate 80, SD Alcohol, Shark Cartilage, Shea Butter, Sorbic Acid, Tetrahexyldecyl Ascorbate, Tocopheryl Acetate, Yucca (Glauca) Root Extract.
* A source of natural metnol

Questions? Comments?

Call 1-800-684-9312 Weekdays between 9am to 5pm CST

Distributed by Pain Management Laboratories, Los Fresnos, TX Made in the USA

Product Label

Dr. Paul Nemiroff's Joint Formula 88 MAX PLUS Pain Relief Cream

NEW MAX PLUS PROFESSIONAL STRENGTH Now with VITAMINS C, D, E - More ANTIOXIDANTS and BOTANICALS
Joint Formula 88 MAX PLUS - "It's the science that makes the difference!"

Dr. Paul Nemiroff's Joint Formula 88 MAX PLUS provides deep penetrating pain relief and is effective in providing temporary relief from minor arthritis, simple backache, muscle aches, strains, bruises, and sprains. Specifically, the ingredients in Joint Formula 88 MAX PLUS are clinically shown to work. Joint Formula 88 MAX PLUS combines the science and power of camphor, natural menthol, glucosamine, chondroitin, aloe, emu oil, shark cartilage, arnica, yucca extract, more vitamins C, D, E to create a fast acting and easy-to-apply cream with no greasy residue. AND...IT REALLY WORKS!
Dr. Paul M. Nemiroff, PhD., M.D. F.A.C.S.
Nationally recognized Surgeon

Award winning Television Medical Correspondent

Recipient of "Humanitarian of the Year Award" for donating his time to operate of refugees

Author of over 100 articles, book chapters, and published research papers.

Dr. Nemiroff is an accomplished head and neck cancer and reconstructive surgeon and received his M.D. from UCLA Medical School with surgical residencies at UCLA-Cedars-Sinai and the University of Florida. Prior to becoming a surgeon he obtained a Ph.D. from Purdue University. He has received over a dozen national awards including Best Surgical Research of the Year from the Society of Head and Neck Surgeons, and awards from the American Cancer Society. He has done hundreds of "on air" medical pieces as a medical correspondent for CBS and ABC television affiliates. Throughout his career, he has performed more than 10,000 surgeries.
Net Wt 4.5 oz. (126 grams) Plus 1.5oz. (42 grams) Travel Size